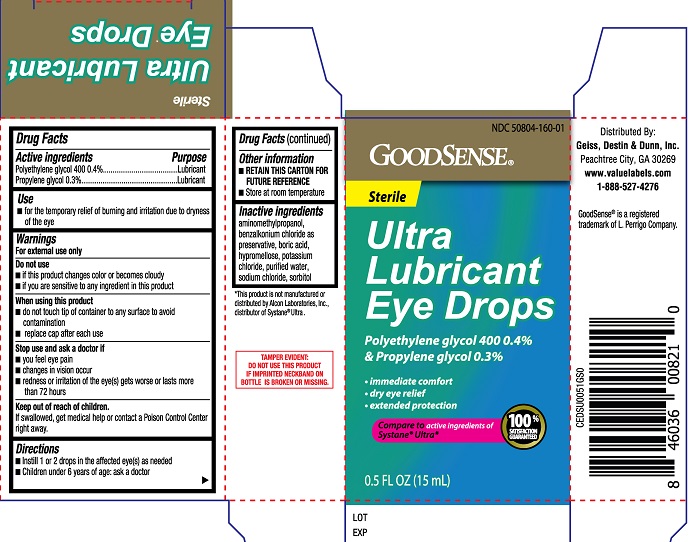 DRUG LABEL: GoodSense Ultra Lubricant Eye Drops
NDC: 50804-160 | Form: SOLUTION
Manufacturer: Geiss, Destin & Dunn, Inc.
Category: otc | Type: HUMAN OTC DRUG LABEL
Date: 20251230

ACTIVE INGREDIENTS: PROPYLENE GLYCOL 0.3 g/100 mL; POLYETHYLENE GLYCOL 400 0.4 g/100 mL
INACTIVE INGREDIENTS: AMINOMETHYLPROPANOL; BENZALKONIUM CHLORIDE; BORIC ACID; HYPROMELLOSES; POTASSIUM CHLORIDE; WATER; SODIUM CHLORIDE; SORBITOL

GoodSense Ultra Lubricant Eye Drops (PLD)

Active ingredients

Polyethylene glycol 400......0.4%

Propylene glycol......0.3%

Purpose

Polyethylene glycol 400......Lubricant

Propylene glycol......Lubricant

Use

- for the temporary relief of burning and irritation due to dryness of the eye

Warnings

For external use only

When using this product

- do not touch tip of container to any surface to avoid contamination
- replace cap after each use

Do not use

- if this product changes color or becomes cloudy
- if you are sensitive to any ingredient in this product

Stop use and ask a doctor if

- you feel eye pain
- changes in vision occur
- redness or irritation of the eye(s) gets worse or lasts more than 72 hours

Keep out of reach of children

If swallowed, get medical help or contact a Poison Control Center right away.

Directions

- Instill 1 or 2 drops in the affected eye(s) as needed
- Children under 6 years of age: ask a doctor

Other information

- RETAIN THIS CARTON FOR FUTURE REFERENCE
- Store at room temperature

Inactive ingredients

aminomethylpropanol, benzalkonium chloride as preservative, boric acid, hypromellose, potassium chloride, sorbitol